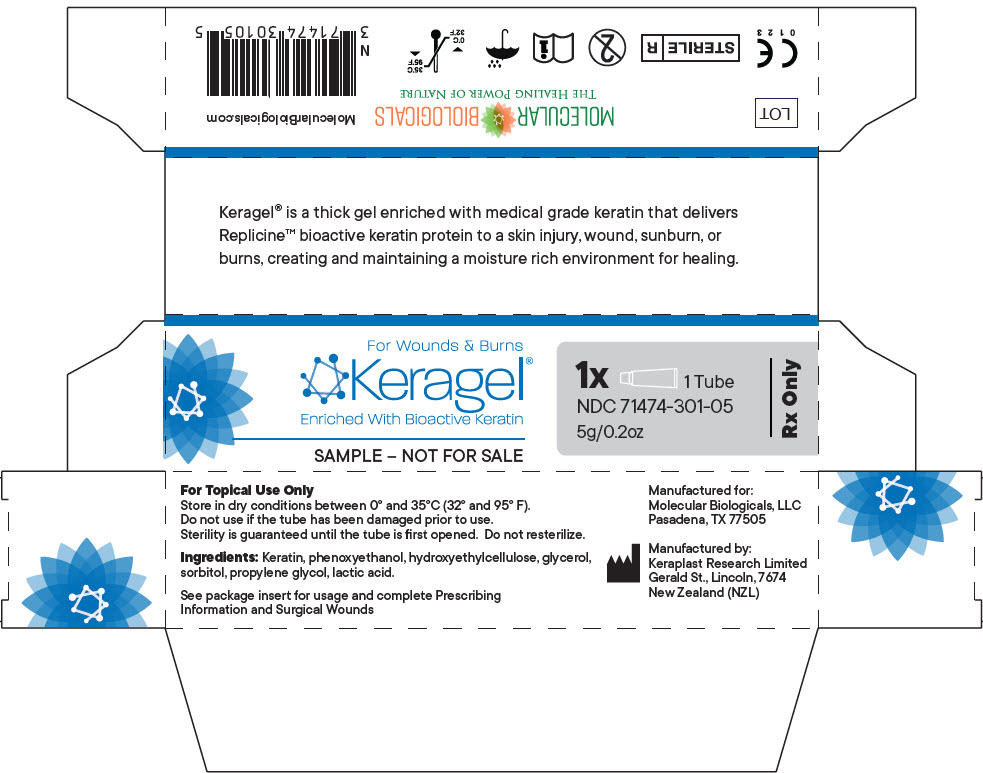 DRUG LABEL: keragel
NDC: 71474-301
Manufacturer: MOLECULAR BIOLOGICALS, LLC
Category: other | Type: PRESCRIPTION MEDICAL DEVICE LABEL
Date: 20180926

ACTIVE INGREDIENTS: Glycerin 100 mg/1 g

keragel®
Wound Gel

STERILE | R

C E
0 1 2 3

Rx Only
Single Use
For Topical Dermatological use only.

Description

keragel® is a keratin enriched gel category dressing utilizing keratin technology to create and maintain a moist wound environment. It is presented sterile in a tube for ease of application.

INDICATIONS FOR USE

keragel® is designed for acute/chronic superficial and partial thickness wounds with dry to medium exudate, such as:

- Venous leg ulcers
- Arterial ulcers
- Diabetic foot ulcers
- Pressure ulcers
- Skin graft donor sites
- Sunburns
- First and Second Degree burns

ATTENTION

If the wound is infected, it is advised that you consult with your physician or health care professional.

DIRECTIONS FOR USE

1. Cleanse and debride the wound in accordance with normal procedures.
2. Ensure that the skin surrounding the wound is dry.
3. The tube is opened using the piercer cap to break the nozzle seal. To ensure sterility, sanitise the piercer cap before using.
4. Apply a 3mm to 6mm (1/8inch to 1/4inch) layer of keragel® to cover the entire wound surface.
5. Cover with an appropriate secondary dressing if needed.

RECOMMENDED CARE

The wound should be inspected daily or as indicated by a physician. For wounds that appear dry more gel should be applied to the area. Wounds should be cleansed regularly and new gel applied.

INGREDIENTS

Keratin, phenoxyethanol, hydroxyethylcellulose, glycerol, sorbitol, propylene glycol, lactic acid.

HOW SUPPLIED

keragel® 20gm individual tube: | NDC 71474-301-20
keragel 5 gm individual tube: | NDC 71474-301-05

STORAGE / PRECAUTIONS

keragel® should be stored in dry conditions between 0° and 35°C (32° and 95° F).

Do not use if the tube has been damaged prior to use. Sterility is guaranteed until the tube is first opened. Do not re-sterilise.

CAUTION: RX ONLY. Federal law restricts this device to sale by or on the order of a physician.

Manufactured for: Molecular Biologicals, LLC
Pasadena, TX 77505 | 1-844-793-9933

EC | REP

Keraplast Research Limited, Gerald St., Lincoln 7674, NZ
Medical Device Consultancy, 7 Pinewood Drive, Ashley Heath,
Market Drayton, Shropshire TF9 4PA, United Kingdom

keragelT® is a registered trademark of
Keraplast Technologies LLC.
The product incorporates patented and/or patent pending
technologies owned by Keraplast Technologies LLC.

Issue Date 8/2017
DWG106/1

PRINCIPAL DISPLAY PANEL - 5 g Tube Box

For Wounds & Burns

Keragel®
Enriched With Bioactive Keratin

1x 1 Tube
NDC 71474-301-05
5g/0.2oz
Rx Only

SAMPLE - NOT FOR SALE